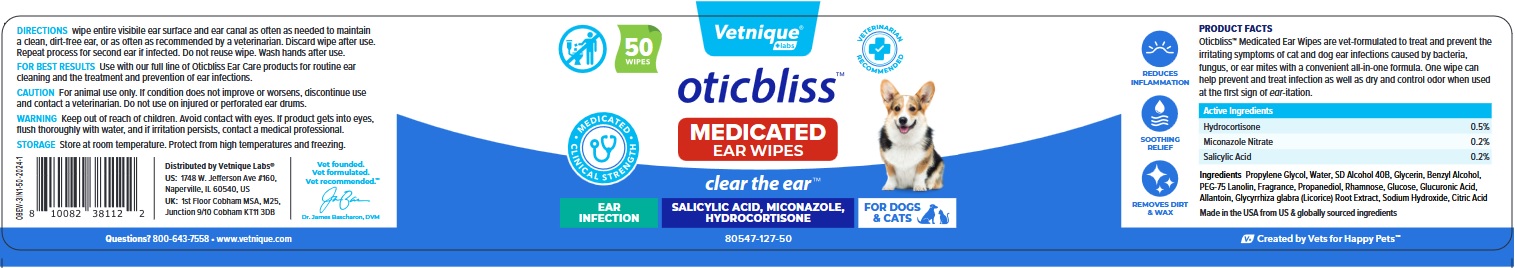 DRUG LABEL: oticbliss MEDICATED EAR WIPES
NDC: 80547-127 | Form: CLOTH
Manufacturer: Vetnique Labs LLC
Category: animal | Type: OTC ANIMAL DRUG LABEL
Date: 20241201

ACTIVE INGREDIENTS: HYDROCORTISONE 5 mg/1 mL; MICONAZOLE NITRATE 2 mg/1 mL; SALICYLIC ACID 2 mg/1 mL
INACTIVE INGREDIENTS: PROPYLENE GLYCOL; WATER; ALCOHOL; GLYCERIN; BENZYL ALCOHOL; PEG-75 LANOLIN; PROPANEDIOL; RHAMNOSE; ANHYDROUS DEXTROSE; GLUCURONIC ACID; ALLANTOIN; GLYCYRRHIZA GLABRA; SODIUM HYDROXIDE; CITRIC ACID MONOHYDRATE

Oticbliss MEDICATED EAR WIPES

PRODUCT FACTS

Oticbliss™ Medicated Ear Wipes are vet-formulated to treat and prevent the irritating symptoms of cat and dog ear infections caused by bacteria, fungus, or ear mites with a convenient all-in-one formula. One wipe can help prevent and treat infection as well as dry and control odor when used at the first sign of ear-irritation.

Active Ingredients

Hydrocortisone 0.5%
Miconazole Nitrate 0.2%
Salicylic Acid 0.2%

Ingredients

Propylene Glycol, Water, SD Alcohol 40B, Glycerin, Benzyl Alcohol, PEG-75 Lanolin, Fragrance, Propanediol, Rhamnose, Glucose, Glucuronic Acid, Allantoin, Glycyrrhiza glabra (Licorice) Root Extract, Sodium Hydroxide, Citric Acid

DIRECTIONS

wipe entire visible ear surface and ear canal as often as needed to maintain a clean, dirt-free ear, or as often as recommended by a veterinarian. Discard wipe after use. Repeat process for second ear if infected. Do not reuse wipe. Wash hands after use.

FOR BEST RESULTS Use with our full line of Oticbliss Ear Care products for routine ear cleaning and the treatment and prevention of ear infections.

CAUTION

For animal use only. If condition does not improve or worsens, discontinue use and contact a veterinarian. Do not use on injured or perforated ear drums.

WARNING

Keep out of reach of children. Avoid contact with eyes. If product gets into eyes, flush thoroughly with water, and if irritation persists, contact a medical professional.

STORAGE

Store at room temperature. Protect from high temperatures and freezing.

VETERINARIAN RECOMMENDED

MEDICATED CLINICAL STRENGTH

clear the ear™

EAR INFECTION

FOR DOGS & CATS

REDUCES INFLAMMATION

SOOTHING RELIEF

REMOVES DIRT AND WAX

Made in the USA from US & globally sourced ingredients

V+ Created by Vets for Happy Pets™

Distributed by Vetnique Labs®
US: 1748 W. Jefferson Ave #160,
Naperville, IL 60540, US

UK: 1st Floor Cobham MSA, M25,
Junction 9/10 Cobham KT11 3DB

Questions? 800-643-7558 • www.vetnique.com

Vet founded.
Vet formulated.
Vet recommended.™